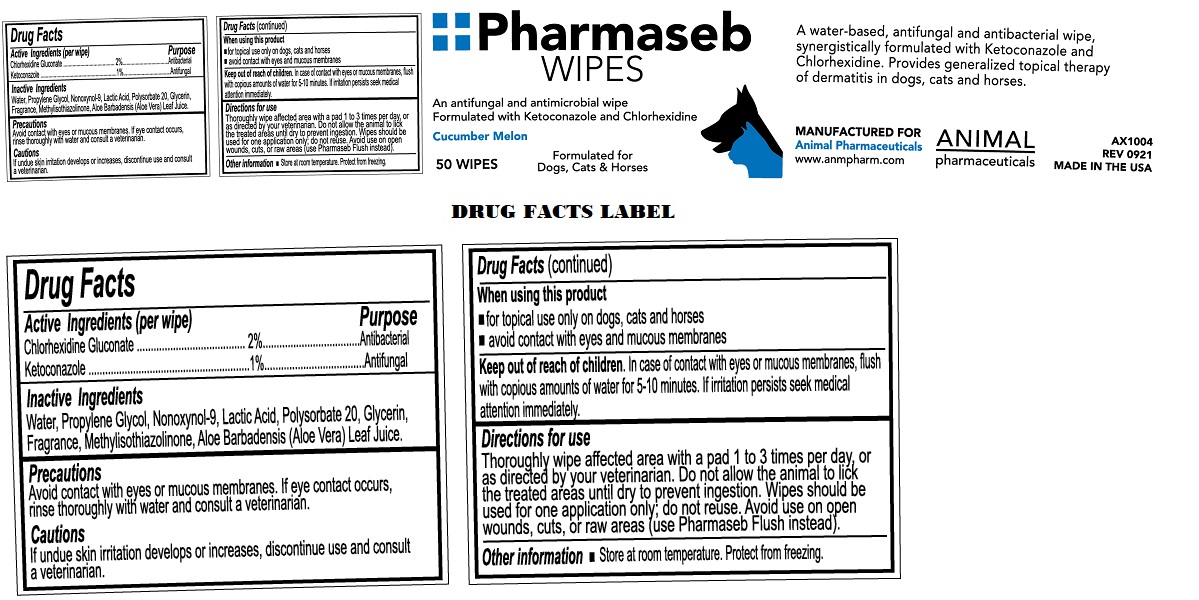 DRUG LABEL: Pharmaseb WIPES
NDC: 68898-119 | Form: CLOTH
Manufacturer: Animal Pharmaceuticals
Category: animal | Type: OTC ANIMAL DRUG LABEL
Date: 20221118

ACTIVE INGREDIENTS: CHLORHEXIDINE GLUCONATE 2 g/100 mL; KETOCONAZOLE 1 g/100 mL
INACTIVE INGREDIENTS: WATER; PROPYLENE GLYCOL; NONOXYNOL-9; LACTIC ACID, UNSPECIFIED FORM; POLYSORBATE 20; GLYCERIN; METHYLISOTHIAZOLINONE; ALOE VERA LEAF

Pharmaseb WIPES

Active Ingredients (per wipe)

Chlorhexidine Gluconate 2%
Ketoconazole 1%

Purpose

Antibacterial
Antifungal

Inactive Ingredients

Water, Propylene Glycol, Nonoxynol-9, Lactic Acid, Polysorbate 20, Glycerin, Fragrance, Methylisothiazolinone, Aloe Barbadensis (Aloe Vera) Leaf Juice.

Precautions

Avoid contact with eyes or mucous membranes. If eye contact occurs, rinse thoroughly with water and consult a veterinarian.

Cautions

If undue skin irritation develops or increases, discontinue use and consult a veterinarian.

When using this product
• for topical use only on dogs, cats and horses
• avoid contact with eyes and mucous membranes

Keep out of reach of children. In case of contact with eyes or mucous membranes, flush with copious amounts of water for 5-10 minutes. If irritation persists seek medical attention immediately.

Directions for use

Thoroughly wipe affected area with a pad 1 to 3 times per day, or as directed by your veterinarian. Do not allow the animal to lick the treated areas until dry to prevent ingestion. Wipes should be used for one application only; do not reuse. Avoid use on open wounds, cuts or raw areas (use Pharmaseb Flush instead).

Other information

• Store at room temperature. Protect from freezing.

An antifungal and antimicrobial wipe

Formulated with Ketoconazole and Chlorhexidine

Cucumber Melon

Formulated for Dogs, Cats & Horses

A water-based, antifungal and antibacterial wipe, synergistically formulated with Ketoconazole and Chlorhexidine. Provides generalized topical therapy of dermatitis in dogs, cats and horses.

MANUFACTURED FOR
Animal Pharmaceuticals
www.anmpharm.com

MADE IN THE USA